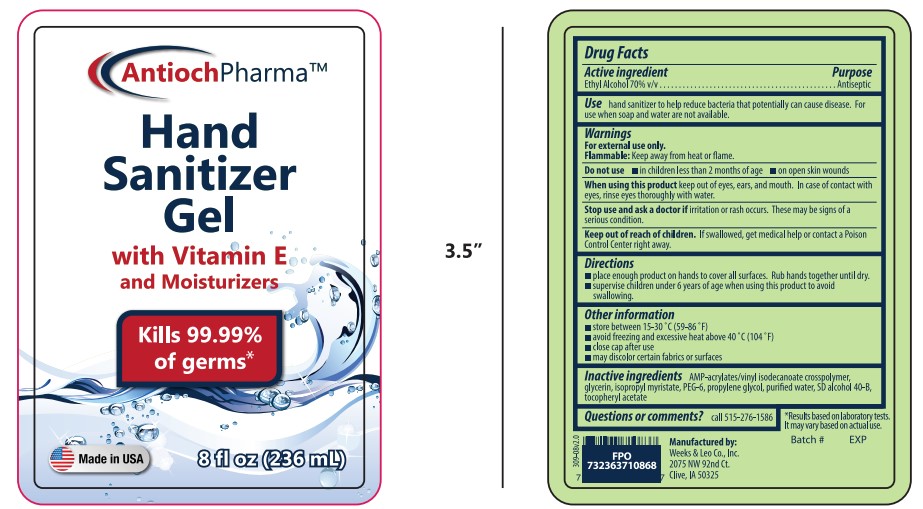 DRUG LABEL: AntiochPharma Rapidgel Hand Sanitizer
NDC: 11383-309 | Form: GEL
Manufacturer: Weeks & Leo
Category: otc | Type: HUMAN OTC DRUG LABEL
Date: 20231212

ACTIVE INGREDIENTS: ALCOHOL 70 mL/100 mL
INACTIVE INGREDIENTS: WATER; GLYCERIN; PROPYLENE GLYCOL; .ALPHA.-TOCOPHEROL ACETATE; ISOPROPYL MYRISTATE; RAPIDGEL EZ1

AntiochPharma Hand Sanitizer Gel Rapidgel

Active Ingredients

Alcohol 70% v/v..................................................................Antiseptic

Purpose

Antiseptic

Uses

hand sanitizer to help reduce bacteria that potentially can cause disease. For use when soap and water are not available.

Warnings

For external use only

Do not use

in children less than 2 months of ageon open skin wounds

When using this product

keep out of eyes, ears, and mouth. In case of contact with eyes, rinse eyes thoroughly with water.

Stop use and ask a doctor if

Irritation or rash occurs. These may be signs of a serious condition.

Keep out of reach of children

If swallowed, get medical help or contact a Poison Control Center right away

Directions

Place enough product on hands to cover all surfaces. Rub hands together until dry.

Supervise children under 6 years of age when using this product to avoid swallowing

Other Information

Store between 15–30 °C (59–86 °F)

Avoid freezing and excessive heat above 40 °C (104 °F)

Close cap after use

May discolor certain fabrics or surfaces

Inactive Ingredients

acrylates/C10–30 alkyl acrylate crosspolymer, aminomethyl propanol, glycerin, isopropyl myristate, propylene glycol, purified water, SD alcohol 40-B, tocopheryl acetate

Package Label

AntiochPharma

Hand Sanitizer

With Vitamin E and Moisturizers

Kills 99.99 %of germs

made in USA